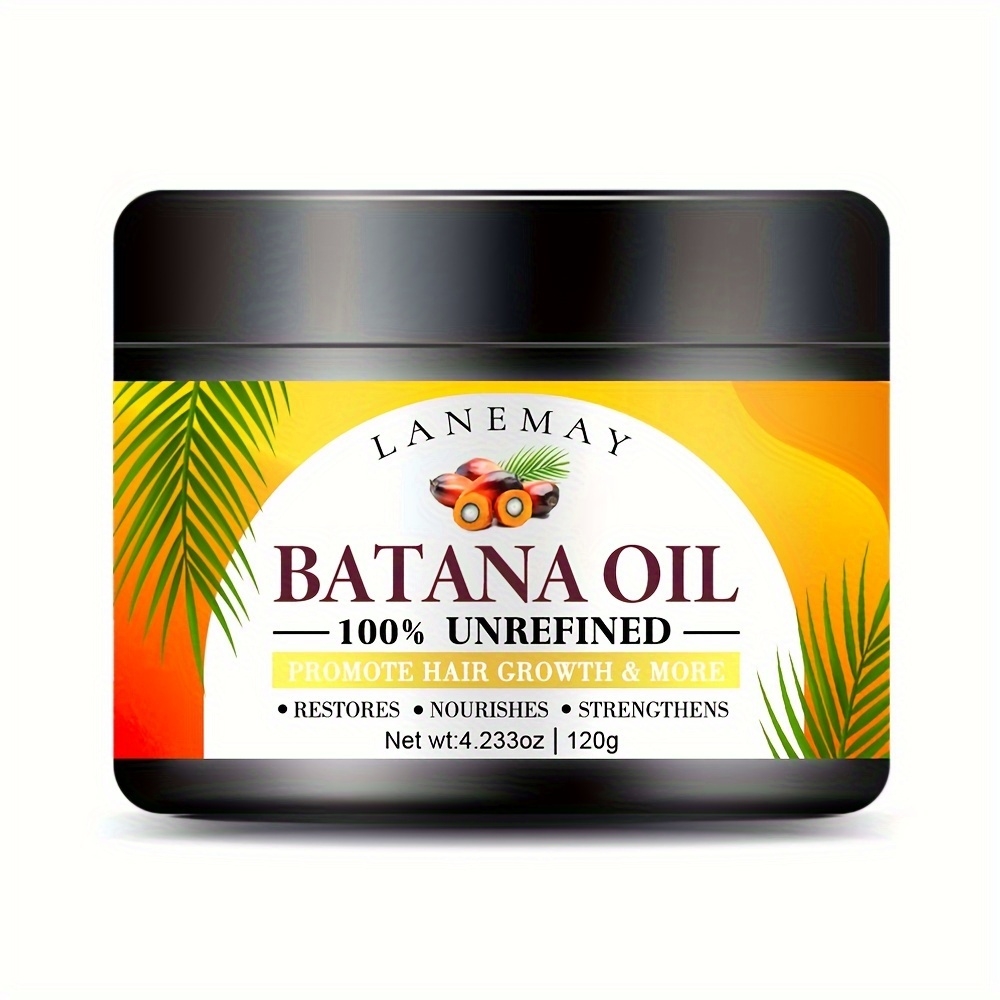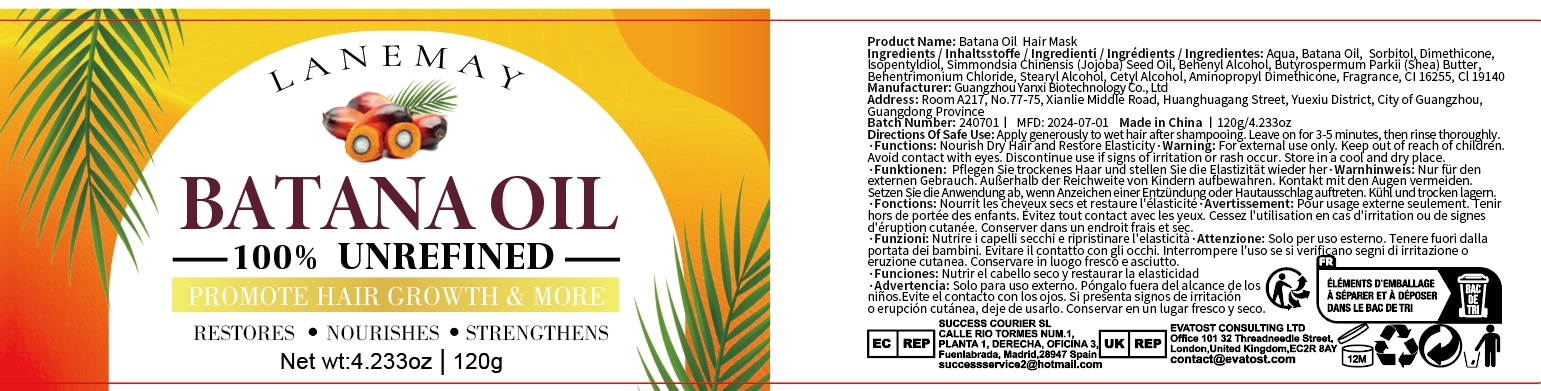 DRUG LABEL: Batana Oil Hair Mask
NDC: 84025-152 | Form: CREAM
Manufacturer: Guangzhou Yanxi Biotechnology Co.. Ltd
Category: otc | Type: HUMAN OTC DRUG LABEL
Date: 20240816

ACTIVE INGREDIENTS: DIMETHICONE 5 mg/120 g; ISOPENTYLDIOL 3 mg/120 g
INACTIVE INGREDIENTS: WATER

DOSAGE AND ADMINISTRATION

Hair mask for nourishing scalp and relieving hair loss problems

WARNINGS

keep out of children

INACTIVE INGREDIENT

Aqua

INDICATIONS AND USAGE

For daily hair and scalp care

Keep out of children

PURPOSE

Keep scalp healthy and effectively solve hair loss problems